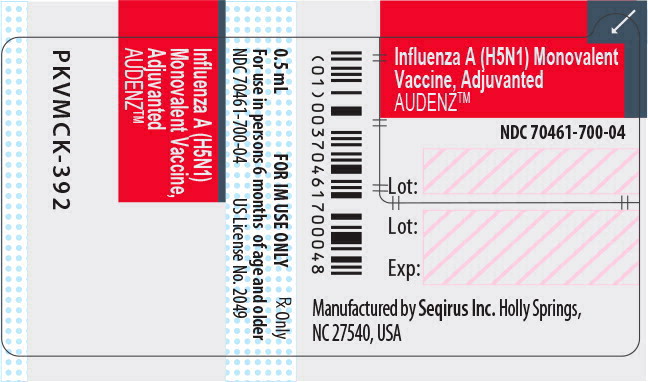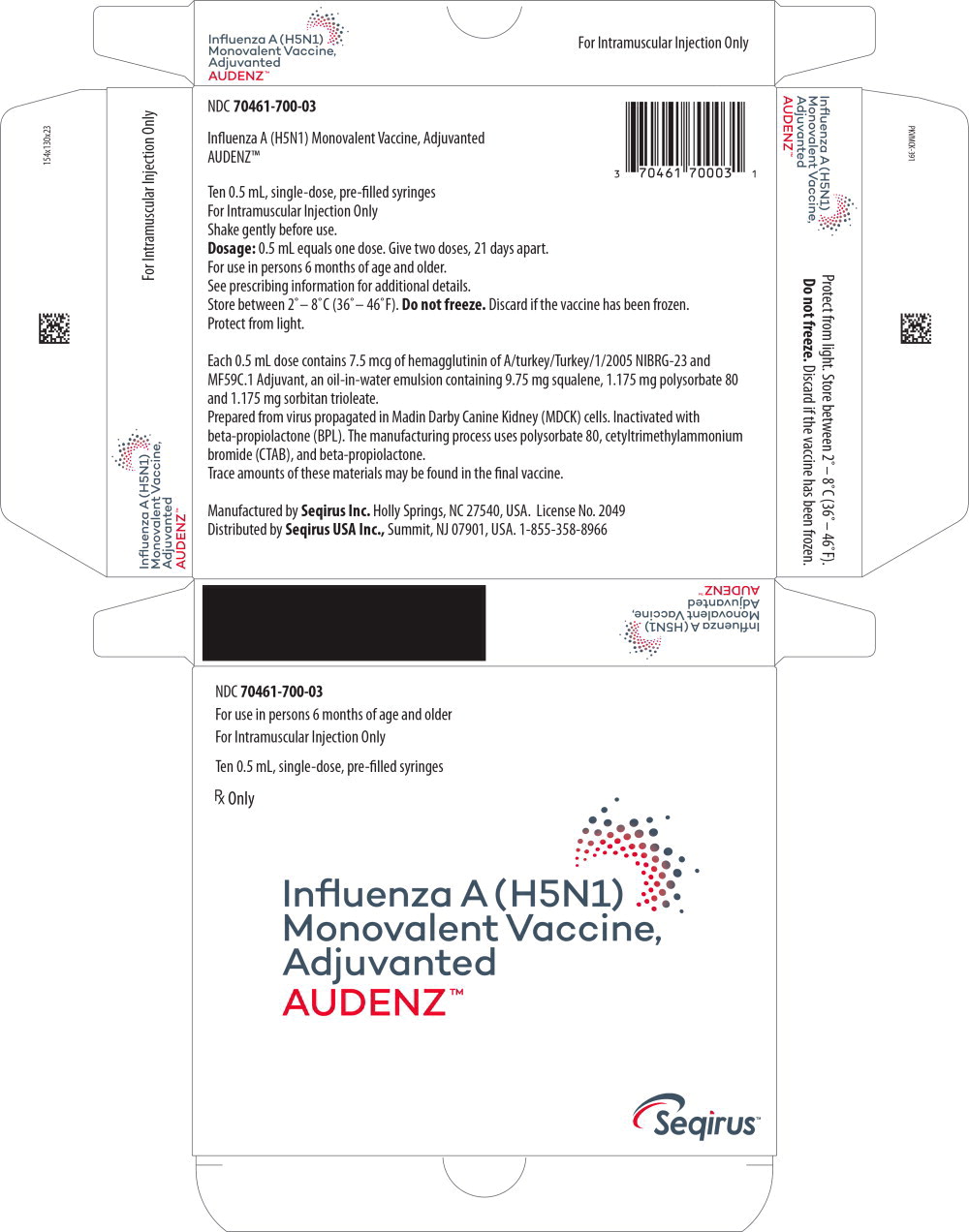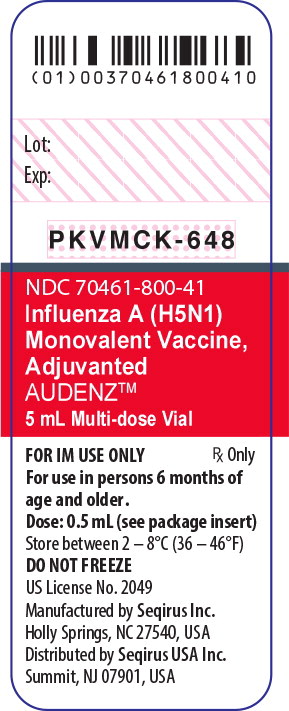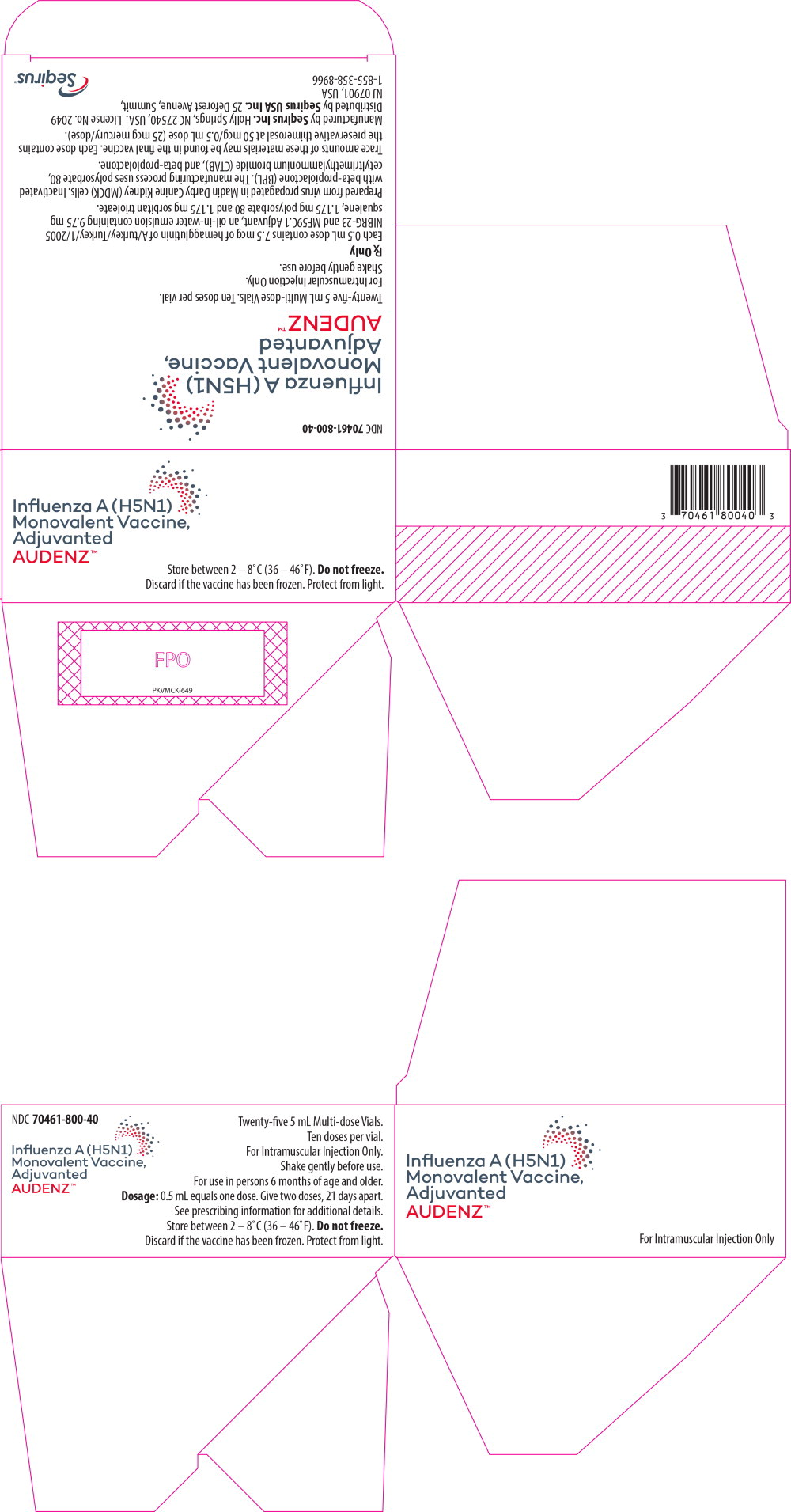 DRUG LABEL: Audenz
NDC: 70461-700 | Form: INJECTION
Manufacturer: Seqirus Inc
Category: other | Type: VACCINE LABEL
Date: 20240806

ACTIVE INGREDIENTS: INFLUENZA A VIRUS H5N1 WHOLE 7.5 ug/0.5 mL
INACTIVE INGREDIENTS: Squalene 9.75 mg/0.5 mL; Polysorbate 80 1.175 mg/0.5 mL; Sorbitan trioleate 1.175 mg/0.5 mL; Trisodium citrate dihydrate 0.66 mg/0.5 mL; Citric acid monohydrate 0.04 mg/0.5 mL; Sodium chloride 4.00 mg/0.5 mL; Potassium chloride 0.1 mg/0.5 mL; MONOBASIC POTASSIUM PHOSPHATE 0.186 mg/0.5 mL; Sodium phosphate, dibasic, dihydrate 0.646 mg/0.5 mL; Magnesium chloride 0.05 mg/0.5 mL; Water

HIGHLIGHTS OF PRESCRIBING INFORMATION

These highlights do not include all the information needed to use AUDENZ™ (Influenza A (H5N1) Monovalent Vaccine, Adjuvanted) safely and effectively. See full prescribing information for AUDENZ.
AUDENZ (Influenza A (H5N1) Monovalent Vaccine, Adjuvanted)
injectable emulsion for intramuscular use
Initial U.S. Approval: 2020

1 INDICATIONS AND USAGE

AUDENZ is an inactivated vaccine indicated for active immunization for the prevention of disease caused by the influenza A virus H5N1 subtype contained in the vaccine. AUDENZ is approved for use in persons 6 months of age and older at increased risk of exposure to the influenza A virus H5N1 subtype contained in the vaccine. (1)

2 DOSAGE AND ADMINISTRATION

For intramuscular injection only

Administer two doses (0.5 mL each) 21 days apart. (2)

3 DOSAGE FORMS AND STRENGTHS

Injectable emulsion is supplied in two presentations:

- 0.5 mL single-dose pre-filled syringe. (3, 11)
- 5 mL multi-dose vial containing 10 doses (each dose is 0.5 mL). (3, 11)

4 CONTRAINDICATIONS

History of a severe allergic reaction (e.g., anaphylaxis) to any component of the vaccine, or after a previous dose of an influenza vaccine. (4, 11)

5 WARNINGS AND PRECAUTIONS

- Hypersensitivity reactions can occur. Appropriate medical treatment and supervision must be available to manage possible anaphylactic reactions following administration of the vaccine. (5.1)
- If Guillain-Barré syndrome has occurred within 6 weeks of receipt of a prior influenza vaccine, the decision to give AUDENZ should be based on careful consideration of potential benefits and risks. (5.2)

6 ADVERSE REACTIONS

- In adults 18 through 64 years of age, the most common (≥ 10%) solicited local and systemic reactions reported in clinical trials were injection site pain (64%), fatigue (25%), headache (25%), malaise (22%), myalgia (14%), arthralgia (10%), and nausea (10%). (6.1)
- In adults 65 years of age and older, the most common (≥ 10%) solicited local and systemic reactions reported in clinical trials were injection site pain (36%), fatigue (20%), malaise (16%), headache (16%), and arthralgia (10%). (6.1)
- In infants and children, 6 months through 5 years of age, the most common (≥ 10%) solicited local and systemic reactions reported in clinical trials were tenderness (56%), irritability (30%), sleepiness (25%), change in eating habits (18%), and fever (16%). (6.1)
- In children 6 through 17 years of age, the most common (≥ 10%) solicited local and systemic reactions reported in clinical trials were injection site pain (68%), myalgia (30%), fatigue (27%), malaise (25%), headache (22%), loss of appetite (14%), nausea (13%), and arthralgia (13%). (6.1)

To report SUSPECTED ADVERSE REACTIONS, contact Seqirus at 1-855-358-8966 or VAERS at 1-800-822-7967 or www.vaers.hhs.gov.

FULL PRESCRIBING INFORMATION

1 INDICATIONS AND USAGE

AUDENZTM is an inactivated vaccine indicated for active immunization for the prevention of disease caused by the influenza A virus H5N1 subtype contained in the vaccine. AUDENZ is approved for use in persons 6 months of age and older at increased risk of exposure to the influenza A H5N1 virus subtype contained in the vaccine.

2 DOSAGE AND ADMINISTRATION

For intramuscular injection only

2.1 Dose and Schedule

Administer two doses of AUDENZ (0.5 mL each), 21 days apart.

2.2 Administration

Shake the syringe gently before use and shake the multi-dose vial gently each time before withdrawing a dose of vaccine. Between multi-dose vial uses, return to the recommended storage conditions of 2° to 8°C (36° to 46°F). AUDENZ has a milky-white appearance. Parenteral drug products should be inspected visually for particulate matter and discoloration prior to administration whenever solution and container permit [see Description (11)]. If either condition exists, AUDENZ should not be administered.

The vaccine should be administered by intramuscular injection. Do not inject the vaccine in the gluteal region or areas where there may be a major nerve trunk. For persons 12 months of age and over, the preferred injection site is the deltoid muscle of the upper arm; for those 6 months through 11 months of age, the preferred injection site is the anterolateral thigh.

3 DOSAGE FORMS AND STRENGTHS

AUDENZ is an injectable emulsion for intramuscular use supplied in two presentations:

- 0.5 mL single-dose pre-filled syringe
- 5 mL multi-dose vial containing 10 doses (each dose is 0.5 mL).

4 CONTRAINDICATIONS

Do not administer AUDENZ to anyone with a history of a severe allergic reaction (e.g., anaphylaxis) to any component of the vaccine [see Description (11)] or after a previous dose of an influenza vaccine.

5 WARNINGS AND PRECAUTIONS

5.1 Hypersensitivity Reactions

Appropriate medical treatment and supervision must be available to manage possible severe allergic reactions (e.g., anaphylaxis) following administration of the vaccine.

5.2 Guillain-Barré Syndrome

If Guillain-Barré syndrome (GBS) has occurred within 6 weeks of receipt of prior influenza vaccine, the decision to give AUDENZ should be based on careful consideration of the potential benefits and risks. The 1976 swine influenza vaccine was associated with an elevated risk of GBS. Evidence for a causal relationship of GBS with other influenza vaccines is inconclusive; if an excess risk exists, it is probably slightly more than 1 additional case per 1 million persons vaccinated.^1

5.3 Limitations of Vaccine Effectiveness

Vaccination with AUDENZ may not protect all recipients.

Immunocompromised persons, including those receiving immunosuppressive therapy, may have a diminished immune response to AUDENZ.

6 ADVERSE REACTIONS

6.1 Clinical Trials Experience

Because clinical trials are conducted under widely varying conditions, adverse reaction rates observed in the clinical trials of a vaccine cannot be directly compared with rates in the clinical trials of another vaccine and may not reflect the rates observed in practice. It is possible that broad use of AUDENZ could reveal adverse reactions not observed in clinical trials.

In adults 18 through 64 years of age, the most common (≥ 10%) solicited local and systemic reactions reported in clinical trials were injection site pain (64%), fatigue (25%), headache (25%), malaise (22%), myalgia (14%), arthralgia (10%) and nausea (10%).

In adults 65 years of age and older, the most common (≥ 10%) solicited local and systemic reactions reported in clinical trials were injection site pain (36%), fatigue (20%), malaise (16%), headache (16%), and arthralgia (10%).

In infants and children, 6 months through 5 years of age, the most common (≥ 10%) solicited local and systemic reactions reported in clinical trials were tenderness (56%), irritability (30%), sleepiness (25%), change in eating habits (18%), and fever (16%).

In children 6 years through 17 years of age, the most common (≥ 10%) solicited local and systemic reactions reported in clinical trials were injection site pain (68%), myalgia (30%), fatigue (27%), malaise (25%), headache (22%), loss of appetite (14%), nausea (13%), and arthralgia (13%).

Adults 18 years of age and older:

Clinical safety data for AUDENZ in adults (18 years of age and older) have been collected from three studies: Study 1 in adults 18 through 64 years of age (NCT01776541); Study 2 in adults 65 years of age and older (NCT01766921), and Study 3, a placebo-controlled trial in adults 18 years of age and older (NCT02839330). Subjects in all studies received 2 doses of AUDENZ, administered intramuscularly 21 days apart. In all three studies, solicited local and systemic adverse reactions were collected for 7 days and unsolicited adverse events were collected for 21 days following each vaccination. Serious adverse events (SAEs), adverse events of special interest (AESIs) (prospectively defined events representing potential immune-mediated conditions), new onset of chronic diseases (NOCDs) (adverse events leading to a new diagnosis of a chronic medical condition), and medically-attended adverse events (MAAEs) (leading to an unscheduled healthcare visit) were collected for one year following the final vaccination in each subject. The safety population includes 3,579 subjects who received at least one dose of AUDENZ. Of these, 1,683 were adults 18 through 64 years of age and 1,896 were adults 65 years of age and older.

Study 3 was a randomized, observer-blind, multicenter, controlled study conducted in the US, in adults 18 years of age and older. Subjects were randomized in a 3:1 ratio to receive two doses of either AUDENZ or saline placebo, 21 days apart. In total, 3,191 subjects (18 through 64 years: N=1,596; 65 years and older: N=1,595) in the safety population received at least one dose of AUDENZ (N=2,395) or placebo (N=796). The mean age of the subjects ≥ 18 years was 58 years, and included 45% male, 84% white, 13% black or African American, 1% Asian, fewer than 1% reported as other racial groups, and 92% non-Hispanic/non-Latinos.

Solicited Reactions:

In Study 3, the most commonly reported (≥ 10%) solicited local and systemic reactions in adults 18 through 64 years within 7 days following administration of AUDENZ were injection site pain (64%), fatigue (25%), headache (25%), malaise (22%), myalgia (14%), arthralgia (10%), and nausea (10%). In adults 65 years of age and older, the most common (≥ 10%) solicited local and systemic reactions reported within 7 days following administration of AUDENZ were injection site pain (36%), fatigue (20%), malaise (16%), headache (16%), and arthralgia (10%).

Tables 1 and 2 present the reported frequencies of pre-specified solicited local and systemic adverse reactions in Study 3, actively collected on standardized diary cards during the seven days following any vaccination (i.e., on the day of vaccination and for six days thereafter). Adults 65 years and older generally reported fewer solicited local and systemic reactions as compared to younger persons. The majority of solicited local and systemic adverse reactions were mild or moderate in intensity. Severe reactions in subjects receiving AUDENZ were reported in 1% or fewer subjects for each reaction. Other than injection site pain which occurred more frequently in AUDENZ recipients as compared to placebo, rates and severity were similar between treatment groups. Frequencies of adverse reactions were higher after the first dose than after the second dose. Most local and systemic reactions occurred within two or three days of vaccination and were less than three days in duration.

Table 1: Percentages of Subjects 18 through 64 Years of Age and 65 Years of Age and Older Reporting Solicited Local Adverse Reactions within 7 Days after Any Vaccination with AUDENZ or Saline Placebo (Study 3a).
Solicited Local Adverse Reactionsb (%) | Adults 18 through 64 years of age AUDENZ (N=1163) c | Adults 18 through 64 years of age Placebo (N=387) c | Adults 65 years of age and older AUDENZ (N=1189) c | Adults 65 years of age and older Placebo (N=397) c
Injection site pain | 64 | 20 | 36 | 10
Erythema ≥25 mm | 0.6 | 0 | 0.4 | 0
Induration ≥25 mm | 0.4 | 0 | 0.7 | 0
Ecchymosis ≥25 mm | 0.3 | 0 | 0.6 | 0.3
a NCT02839330
b Severe (Grade 3) reactions of each type were reported in 1% or fewer subjects receiving AUDENZ; severe (Grade 3) reactions of each type were also reported in the placebo group at similar percentages. Grade 3 local pain is that which prevents daily activity; Grade 3 injection site erythema, induration and ecchymosis include any ≥ 100 mm in diameter.
c Number of subjects in the Solicited Safety Population (subjects who were vaccinated and provided any solicited safety data, excluding the 30-minute post-vaccination observation period) for each dose group.

Table 2: Percentages of Subjects 18 through 64 Years of Age and 65 Years of Age and Older Reporting Solicited Systemic Adverse Reactions within 7 Days after Any Vaccination with AUDENZ or Saline Placebo (Study 3a).
Solicited Systemic Adverse Reactionsb (%) | Adults 18 through 64 years of age AUDENZ (N=1163) c | Adults 18 through 64 years of age Placebo (N=387) c | Adults 65 years of age and older AUDENZ (N=1189) c | Adults 65 years of age and older Placebo (N=397) c
Fatigue | 25 | 21 | 20 | 19
Headache | 25 | 23 | 16 | 16
Malaise | 22 | 12 | 16 | 12
Myalgia | 14 | 11 | 9 | 8
Arthralgia | 10 | 9 | 10 | 9
Nausea | 10 | 11 | 7 | 6
Loss of appetite | 8 | 9 | 6 | 6
Chills | 4 | 4 | 4 | 3
Fever (≥100.4°F) | 0.6 | 2 | 0.7 | 0.3
a NCT02839330
b Severe (Grade 3) reactions of each type were reported in 1% or fewer subjects receiving AUDENZ; severe (Grade 3) reactions of each type were also reported in the placebo group at similar percentages. Grade 3 fever is any oral temperature ≥ 102.2°F; for other systemic reactions, Grade 3 is that which prevents daily activity or leads to decreased oral intake.
c Number of subjects in the Solicited Safety Population (subjects who were vaccinated and provided any solicited safety data, excluding the 30-minute post-vaccination observation period) for each dose group.

Unsolicited Adverse Events:

In Study 3, the proportion of subjects 18 years of age and older who reported unsolicited AEs in the 21 days after each vaccination was similar between AUDENZ and placebo groups (23% vs. 22%). The frequencies and types of unsolicited adverse events were similar between treatment groups. Across both age and treatment groups, most events were mild to moderate in severity and considered unrelated to vaccinations. The following unsolicited AE was reported as possibly or probably related at a rate ≥ 1% in both AUDENZ and placebo groups: Injection site bruising (1.5%).

Serious Adverse Events (SAEs)

In Study 3, fatal and non-fatal SAEs reported in the 12 months following vaccinations among adults 18 through 64 years of age occurred in 2.9% of subjects who received AUDENZ and 3.3% of subjects who received placebo. SAE rates among adults 65 years of age and older were 10.5% in subjects administered AUDENZ and 15.3% in subjects who received placebo. Fatal SAEs included 11 (0.5%) AUDENZ recipients and 1 (0.1%) placebo recipients. No SAEs were assessed as being related to AUDENZ.

Studies 1 and 2 did not have a placebo or active comparator control for comparison of safety. Four deaths occurred in Study 1 (subjects 18 through 64 years) and two in Study 2 (subjects ≥ 65 years), none assessed as related to AUDENZ. In the 12 months following vaccinations, SAEs (fatal and non-fatal) occurred in a total of n=28 (3%) of all subjects in Study 1. SAEs occurred in a total of n=96 (7%) subjects in Study 2. In both Studies 1 and 2, all SAEs appeared unrelated to study treatment.

Adverse Events of Special Interest (AESIs)

In Studies 1, 2, and 3 combined, AESIs, such as new onset neuroinflammatory and immune mediated diseases, were assessed in the studies using a predefined list. The percentages of subjects with an AESI at any time after vaccination was 0.2% among adults 18 through 64 years of age and 0.4% among adults 65 years of age and older who received AUDENZ. In the placebo group, 1.8% of adults 65 years and older reported AESIs while there were no AESIs reported for adults 18 through 64 years. No AESIs were assessed as related to AUDENZ.

New Onset of Chronic Diseases and Medically-Attended Adverse Events

In Studies 1, 2 and 3 combined, NOCDs (9.7% vs 9.2%) and MAAEs (47.1% vs 46.0%) occurred with similar frequencies between AUDENZ and placebo recipients, respectively, with larger proportions of these events occurring in subjects ≥ 65 years. No large imbalances in types of events were observed between treatment groups.

Children and adolescents 6 months through 17 years of age:

Clinical safety data for AUDENZ in children 6 months through 17 years of age were collected in Study 4.

Study 4 was an observer-blind, multicenter study conducted in the U.S. and Thailand in children 6 months through 17 years of age (NCT 01776554). A total of 329 subjects in the safety population received two doses of AUDENZ administered intramuscularly 21 days apart. Solicited local (injection site) and systemic adverse reactions were collected for seven days (the day of vaccination and for six days thereafter) following each vaccination in all children, divided into two age cohorts (6 months through 5 years [N=160], and 6 years through 17 years of age [N=163]). Unsolicited adverse events were collected for 21 days following each vaccination for children 6 months through 17 years of age. SAEs, AESIs, NOCDs, and MAAEs were monitored for one year after the last vaccination.

The mean age of subjects in Study 4 was 79 months (6.5 years), 54% were male, 72% were Asian, 22% white, 4% black or African American, 2% other, <1% American Indian or Alaska native, and 96% were non-Hispanic/non-Latino. A total of 72% of the safety population was enrolled in Thailand and 28% in the U.S.

Solicited Reactions:

The majority of solicited local and systemic adverse reactions reported in each age group of children 6 months through 5 years and 6 years through 17 years were mild or moderate in intensity, and resolved within a few days. The proportions of subjects who reported solicited local or systemic reactions were lower following the second vaccination as compared to the first.

The most common (≥10%) solicited local and systemic reactions within 7 days following administration of AUDENZ in children 6 months through 5 years of age were tenderness (56%), irritability (30%), sleepiness (25%), change in eating habits (18%) and fever (16%). The most common (≥10%) solicited local and systemic reactions within 7 days following administration of AUDENZ in children 6 years through 17 years of age were pain (68%), myalgia (30%), fatigue (27%), malaise (25%), headache (22%), loss of appetite (14%), nausea (13%), and arthralgia (13%).

The proportions of children 6 months through 5 years who reported solicited adverse reactions are presented in Tables 3 and 4.

Table 3: Percentage of Children 6 Months through 5 Years of Age with Solicited Adverse Local Reactions within 7 days after Any Vaccination with AUDENZ (Study 4a)
Solicited Local Adverse Reactionsb | AUDENZ (N=159) c%
Tenderness (Any) | 56
Tenderness (Severe) | 1
Erythema (≥ 10 mm) | 3
Erythema (≥ 50 mm) | 0
Induration (≥ 10 mm) | 1
Induration (≥ 50 mm) | 0
Ecchymosis (≥ 10 mm) | 0
Ecchymosis (≥ 50 mm) | 0
a NCT01776554
b Any erythema, induration or ecchymosis were defined as a measured diameter ≥ 10 mm. Severe (Grade 3) reactions were defined as follows: Tenderness = cried when injected limb was moved; Erythema, Induration and Ecchymosis = diameter ≥ 50 mm.
c N = number of subjects in the Solicited Safety Population who were vaccinated and provided solicited local adverse event safety data, excluding the 30-minute post-vaccination observation period).

Table 4: Percentage of Children 6 Months through 5 Years of Age with Solicited Adverse Systemic Reactions within 7 days after Any Vaccination with AUDENZ (Study 4a)
Solicited Systemic Adverse Reactionsb | AUDENZ (N=159-160) c%
Irritability (Any) | 30
Irritability (Severe) | 1
Sleepiness (Any) | 25
Sleepiness (Severe) | 0
Change in eating habits (Any) | 18
Change in eating habits (Severe) | 0
Fever (≥ 100.4° F) | 16
Fever (≥ 102.1° F) | 2
a NCT01776554
b Severe (Grade 3) reactions were defined as follows: Irritability = unable to console; Sleepiness = sleeps most of the time and it is hard to arouse him/her; Change in eating habits = missed more than 2 feeds; Fever = body temperature ≥102.1°F.
c N = number of subjects in the Solicited Safety Population who were vaccinated and provided solicited systemic adverse event safety data, excluding the 30-minute post-vaccination observation period).

The reported frequencies of solicited adverse reactions in children 6 years through 17 years of age are presented in Tables 5 and 6.

Table 5: Percentage of Children 6 through 17 Years of Age with Solicited Local Adverse Reactions within 7 days after Any Vaccination with AUDENZ (Study 4a)
Solicited Local Adverse Reactionsb | AUDENZ (N=163) c%
Injection site pain (Any) | 68
Injection site pain (Severe) | 1
Erythema (≥ 25 mm) | 1
Erythema (≥ 100 mm) | 0
Induration (≥ 25 mm) | 2
Induration (≥ 100 mm) | 0
Ecchymosis (≥ 25 mm) | 0
Ecchymosis (≥ 100 mm) | 0
a NCT01776554
b Severe (Grade 3) reactions were defined as follows: Pain = prevented daily activity; Erythema, Induration and Ecchymosis = diameter > 100 mm; .
c Number of subjects in the Solicited Safety Population who were vaccinated and provided solicited local adverse event safety data, excluding the 30-minute post-vaccination observation period).

Table 6: Percentage of Children 6 through 17 Years of Age with Solicited Systemic Adverse Reactions within 7 days after Any Vaccination with AUDENZ (Study 4a)
Solicited Systemic Adverse Reactionsb | AUDENZ (N=162-163) c%
Myalgia (Any) | 30
Myalgia (Severe) | 0
Fatigue (Any) | 27
Fatigue (Severe) | 1
Malaise (Any) | 25
Malaise (Severe) | 1
Headache (Any) | 22
Headache (Severe) | 0
Loss of appetite (Any) | 14
Loss of appetite (Severe) | 1
Nausea (Any) | 13
Nausea (Severe) | 1
Arthralgia (Any) | 13
Arthralgia (Severe) | 0
Fever (≥ 100.4°F) | 4
Fever (≥ 102.1°F) | 1
a NCT01776554
b Severe (Grade 3) reactions were defined as follows: Myalgia, Fatigue, Malaise, Headache, Nausea and Arthralgia = Prevents daily activity; Loss of appetite = Decreased oral intake with weight loss.
c Number of subjects in the Solicited Safety Population who were vaccinated and provided solicited systemic adverse event safety data, excluding the 30-minute post-vaccination observation period).

Unsolicited Adverse Events:

In children 6 months through 17 years of age (N=329), 26% of subjects who received AUDENZ reported at least one unsolicited adverse event within 21 days after any vaccination. The most common unsolicited AEs (≥ 2%) among all subjects were upper respiratory infection (8%), pyrexia (5%), nasopharyngitis (4%) and vomiting (2%). Most AEs were mild or moderate in severity. One child was discontinued from the second vaccination due to a non-serious AE (pyrexia on Day 3) assessed as possibly related to study vaccine.

Serious Adverse Events

A total of 8 (2%) children 6 months through 17 years of age in the safety population (N=326) experienced SAEs during the study. SAEs consisted of events typical for a pediatric population and were assessed as unrelated to study vaccine. No deaths were reported during the study.

Adverse Events of Special Interest

No AESIs were reported during the study.

New Onset of Chronic Diseases and Medically-Attended Adverse Events

No AUDENZ recipients reported NOCDs during the study. MAAEs were reported by 34% of all subjects and were typical of events that occur in a pediatric population. The most common MAAEs were categorized as infections and infestations (reported by 26% of subjects).

6.2 Postmarketing Experience

There is no postmarketing experience following administration of AUDENZ.

The following adverse events have been reported during postmarketing use of influenza vaccines that contain the same MF59® adjuvant or share the same manufacturing platform as the influenza antigen in AUDENZ.

Because spontaneously reported events are reported voluntarily from a population of uncertain size, it is not always possible to reliably estimate their incidence or to establish a causal relationship to the vaccine.

Blood and lymphatic system disorders: Lymphadenopathy.

Immune system disorders: Hypersensitivity reactions including angioedema and anaphylaxis.

Nervous system disorders: Bell's Palsy, convulsions, including febrile convulsion, demyelination, encephalitis, Guillain-Barré Syndrome, neuritis, paresthesia, syncope.

Skin and subcutaneous tissue disorders: Urticaria, pruritis, non-specific rash.

Musculoskeletal and connective tissue disorders: Muscular weakness.

7 DRUG INTERACTIONS

7.1 Concomitant Vaccine Administrations

No data are available to evaluate the concomitant administration of AUDENZ with other vaccines.

7.2 Concurrent Use with Immunosuppressive Therapies

Immunosuppressive or corticosteroid therapies may reduce the immune response to AUDENZ.

8 USE IN SPECIFIC POPULATIONS

8.1 Pregnancy

Risk Summary

All pregnancies have a risk of birth defect, loss, or other adverse outcomes. In the U.S. general population, the estimated background risk of major birth defects and miscarriage in clinically recognized pregnancies is 2% to 4% and 15% to 20%, respectively.

There are insufficient data on AUDENZ in pregnant women to inform vaccine-associated risks in pregnancy.

A developmental toxicity study was performed in female rabbits administered AUDENZ prior to mating and during gestation. A 0.5 mL dose was injected on each occasion (a single human dose is 0.5 mL). This study revealed no evidence of harm to the fetus or offspring due to AUDENZ [see 8.1 Data].

Clinical Considerations

Disease-associated Maternal and/or Embryo/Fetal Risk

There is limited information on the risk of influenza A (H5N1) infection in pregnant women. However, pregnant women infected with pandemic H1N1 or with seasonal influenza are at increased risk of severe illness associated with influenza infection compared to non-pregnant women. Pregnant women with influenza may be at increased risk for adverse pregnancy outcomes, including preterm labor and delivery.

Data

Animal Data

In a developmental toxicity study, female rabbits were administered 0.5 mL of AUDENZ by intramuscular injection 1 and 3 weeks prior to mating, and on gestation days 7 and 20. No vaccine-related fetal malformations or variations and no adverse effects on pre-weaning development were observed in the study.

Lactation

Risk Summary

It is not known whether AUDENZ is excreted in human milk. Data are not available to assess the effects of AUDENZ on the breastfed infant or on milk production/excretion.

The developmental and health benefits of breastfeeding should be considered along with the mother's clinical need for AUDENZ and any potential adverse effects on the breastfed child from AUDENZ or from the underlying maternal condition. For preventive vaccines, the underlying maternal condition is susceptibility to disease prevented by the vaccine.

8.4 Pediatric Use

Safety and effectiveness of AUDENZ in infants younger than 6 months have not been established.

8.5 Geriatric Use

Two clinical studies of AUDENZ included a total of 1,896 subjects 65 years of age and older administered AUDENZ. Of these, 533 subjects were 75 years of age and older.

Subjects 65 years of age and older had a lower immune response to AUDENZ than subjects 18 through 64 years; the pre-specified targets for the immunogenicity endpoints were met in the geriatric subjects [see Clinical Studies (14)]. No clinically relevant differences in safety between subjects 65 years of age and older and younger subjects were observed [see Adverse Reactions (6)].

11 DESCRIPTION

AUDENZ, a sterile injectable emulsion for intramuscular use, is an inactivated, monovalent, subunit influenza vaccine prepared from virus propagated in Madin Darby Canine Kidney (MDCK) cells, a continuous cell line. These cells were adapted to grow freely in suspension in culture medium. The virus is inactivated with ß-propiolactone, disrupted by the detergent cetyltrimethylammonium bromide and purified through several process steps. The influenza antigen contained in AUDENZ is manufactured according to the same process as that used to produce the antigens contained in FLUCELVAX® and FLUCELVAX® QUADRIVALENT, which are unadjuvanted seasonal influenza vaccines licensed for use in the United States.

AUDENZ is a milky-white emulsion. Each 0.5 mL dose is formulated to contain 7.5 mcg of hemagglutinin (HA) of the influenza virus strain A/turkey/Turkey/1/2005 NIBRG-23, a reverse genetics-derived reference strain supplied by the National Institute for Biological Standards and Control (NIBSC), and MF59C.1 adjuvant (MF59), a squalene-based oil-in-water emulsion (9.75 mg squalene, 1.175 mg polysorbate 80, 1.175 mg sorbitan trioleate, 0.66 mg sodium citrate dihydrate and 0.04 mg citric acid monohydrate), at pH 6.5-7.7.

Each dose of AUDENZ may also contain residual amounts of protein other than HA (≤ 30 mcg) including MDCK cell protein (≤3.15 mcg), MDCK cell DNA (≤ 10 ng), additional polysorbate 80 (≤ 0.375 mg), cetyltrimethylammonium bromide (≤ 4.5 mcg), and ß-propiolactone (≤ 0.1 mcg), which are used in the manufacturing process.

AUDENZ contains no antibiotics. AUDENZ 0.5 mL single-dose pre-filled syringes contain no preservative.

AUDENZ 5 mL multi-dose vials contain thimerosal, a mercury derivative, added as a preservative. Each 0.5 mL dose from the multi-dose vial contains 25 mcg mercury.

The tip caps and plungers of the pre-filled syringes and the multi-dose vial stopper are not made with natural rubber latex.

12 CLINICAL PHARMACOLOGY

12.1 Mechanism of Action

A specific post-vaccination hemagglutination-inhibition (HI) antibody titer has not been correlated with protection from H5N1 influenza illness; however, HI titers have been used as a measure of influenza vaccine activity. In some human challenge studies with other influenza virus strains, antibody titers of ≥ 1:40 have been associated with protection from influenza illness in up to 50% of subjects [see References (2, 3)].

13 NONCLINICAL TOXICOLOGY

13.1 Carcinogenesis, Mutagenesis, Impairment of Fertility

AUDENZ has not been evaluated for carcinogenic or mutagenic potential, or for impairment of male fertility in animals. Administration of AUDENZ did not affect female fertility in a rabbit developmental toxicity study [see Pregnancy (8.1)].

14 CLINICAL STUDIES

The influenza antigen contained in AUDENZ is manufactured according to the same process as that used to produce the antigens contained in FLUCELVAX and FLUCELVAX QUADRIVALENT, which are unadjuvanted seasonal influenza vaccines licensed in the United States. Effectiveness of AUDENZ was demonstrated based on serum HI antibody responses to AUDENZ and effectiveness of FLUCELVAX, including a demonstration of efficacy of FLUCELVAX in the prevention of influenza disease in adults 18 through 49 years of age, and in children and adolescents 2 years through 17 years of age, and demonstration of non-inferior immunogenicity of Flucelvax as compared to a U.S.-licensed comparator inactivated quadrivalent influenza vaccine in children 6 through 23 months.

14.1 Immunological Evaluation

Adults 18 years of age and older:

Study 3 was a phase 3, randomized, observer-blind, multicenter, placebo-controlled trial conducted in the United States in 3,196 adults 18 years of age and older, who were stratified by age and randomized 3:1 to receive either two doses of AUDENZ or saline placebo, 21 days apart. The mean age of all enrolled subjects was 58 years, 55% were female, 84% were white, 13% black or African American, 1% Asian, and 92% non-Hispanic/non-Latino. In total, 2,988 subjects (18 through 64 years N=1,488; ≥ 65 years N=1,500) in the per protocol population received both doses of AUDENZ (N=2,249) or placebo (N=739). HI antibody titers against the A/turkey/Turkey/1/2005 (H5N1) strain were evaluated in sera obtained 21 days after the second dose.

HI titers were assessed according to prespecified criteria for the proportion of subjects with seroconversion (defined as a pre-vaccination HI titer < 1:10 and post-vaccination HI titer ≥ 1:40 or a pre-vaccination HI titer ≥ 1:10 and ≥ 4-fold increase in HI titer) and the proportion of subjects with a post-vaccination HI titer ≥ 1:40. Assessment of the proportion of subjects with seroconversion or an HI titer ≥ 1:40 after vaccination was assessed by age group (18 through 64 years and ≥ 65 years). Success criteria required the lower bound of the 2-sided 95% CI for the proportion of subjects with seroconversion, to be ≥40% for subjects 18 through 64 years, and ≥ 30% for subjects ≥ 65 years of age. For the proportion of subjects with an HI titer ≥ 1:40, the lower bound of the 2-sided 95% CI was required to be ≥ 70% for subjects 18 through 64 years of age, and ≥ 60% for subjects ≥ 65 years of age.

In subjects 18 through 64 years of age and in subjects ≥ 65 years of age, the prespecified criteria for proportion of subjects with seroconversion and an HI titer ≥ 1:40 were met 21 days after the second vaccination (Table 7).

Table 7. Seroconversion Rates and Percentage of Subjects with HI Titers ≥ 1:40 following AUDENZ or Placebo (21 Days after Second Dose) by Age Cohort – Per Protocol Seta (Study 3b)
Immune Response | Adults 18 through 64 years of age AUDENZ (N=1076) | Adults 18 through 64 years of age Placebo (N=349) | Adults 65 years of age and older AUDENZ (N=1080) | Adults 65 years of age and older Placebo (N=351)
% Seroconversionc (95% CI) | 79.9% (77.4, 82.3) | 0.3% (0.0, 1.6) | 54.0% (51.0, 57.0) | 1.7% (0.6, 3.7)
% HI Titer ≥ 1:40 d (95% CI) | 95.0% (93.4, 96.2) | 8.5% (5.9, 12.1) | 85.7% (83.3, 87.9) | 20.8% (16.6, 25.8)
Abbreviations: N=number of subjects in each group, Per Protocol Set; HI=hemagglutinin inhibition; CI=confidence interval.
a Per Protocol Set: subjects who received 2 doses of AUDENZ according to the study protocol
b ClinicalTrials.gov identifier: NCT02839330
c Seroconversion is defined as a pre-vaccination HI titer < 1:10 and post-vaccination HI titer ≥ 1:40 or a pre-vaccination HI titer ≥ 1:10 and ≥ 4-fold increase in HI titer. Success criteria for seroconversion: For subjects 18 to < 65 years, the lower bound (LB) of the 95% CI for the Seroconversion must be ≥ 40%; for subjects ≥ 65 years, the LB of the 95% CI for the Seroconversion must be ≥ 30%.
d %HI titer ≥ 1:40 is the percentage of subjects with an HI titer of at least 1:40 at 21 days following the second vaccination. Success criteria for %HI ≥ 1:40: For subjects 18 to < 65 years, the lower bound (LB) of the 95% CI for the % HI ≥40 must be ≥ 70%; for subjects ≥ 65 years, the LB of the 95% CI for the % HI ≥40 must be ≥60%.

Children and adolescents 6 months through 17 years of age:

Study 4 was an observer-blind multicenter study conducted in Thailand and the U.S. in children 6 months through 17 years of age, stratified by age (6 through 35 months, 3 through 8 years, and 9 through 17 years). A total of 289 subjects in the full analysis population received two doses of AUDENZ, 21 days apart.

The mean age of the subjects was 79.6 months; 55% of the subjects were male, 72% of the participants were Asian, 23% were White, and 3% were Black or African American, and 96% were non-Hispanic/non-Latino. A total of 72% of subjects were from Thailand and 28% from the U.S. HI antibody titers against the A/turkey/Turkey/1/2005 (H5N1) strain were evaluated in sera obtained 21 days after the second dose in the overall full analysis population and in the three age cohorts.

The co-primary endpoints for the overall full analysis population were: 1) the proportion of subjects with seroconversion and 2) the proportion of subjects with an HI titer of ≥ 1:40 after vaccination, each were evaluated according to prespecified criteria. Success criteria applied to the co-primary endpoint analyses were as follows: 1) for the proportion of subjects with seroconversion (defined as a pre-vaccination HI titer <1:10 and post-vaccination HI titer ≥ 1:40, or a pre-vaccination HI titer ≥ 1:10 and ≥ 4-fold increase in HI titer), the lower bound of the 2-sided 97.5% CI should be ≥ 40%; and 2) for the proportion of subjects with an HI titer ≥ 1:40, the lower bound of the 2-sided 97.5% CI should be ≥ 70%. Similar criteria, using 95% CIs, were applied to secondary analyses of each age subgroup.

In both the overall full analysis population and in all three age subgroups, the prespecified criteria for the proportions of subjects with seroconversion and an HI titer ≥ 1:40 were met at 21 days after the second vaccination with AUDENZ. These data are presented in Table 8.

Table 8. Seroconversion Rates and Percentage of Subjects with HI Titers ≥ 1:40 at 21 days following the second dose of AUDENZ – Full Analysis Seta (Study 4b)
Immune Response | Overall Population 6 months through 17 years (N=279 – 287) | Age Subgroup 6 months through 35 months (N= 84 – 91) | Age Subgroup 3 years through 8 years (N= 93 – 94) | Age Subgroup 9 years through 17 years (N= 102)
% Seroconversionc (97.5% CI, overall) (95% CI, subgroups) | 96% (93, 98) | 99% (94, 100) | 98% (92, 100) | 92% (85, 97)
% HI Titer ≥ 1:40 d (97.5% CI, overall) (95% CI subgroups) | 96% (92, 98) | 98% (92, 100) | 98% (93, 100) | 92% (85, 97)
Abbreviations: HI=hemagglutinin inhibition; CI=confidence interval; N=number of subjects in the FAS at the Day 43 timepoint.
a FAS: Full Analysis Set, subjects who received at least one dose of AUDENZ and provided immunogenicity data at the relevant timepoints, i.e. at Days 1 and 43 for the primary analysis.
b ClinicalTrials.gov identifier: NCT01776554.
c Seroconversion is defined as a prevaccination HI titer < 1:10 and postvaccination HI titer ≥ 1:40 or a prevaccination HI titer ≥ 1:10 and ≥ 4-fold increase in HI titer. Success criteria for seroconversion: For subjects 6 months through 17 years overall, the lower bound (LB) of the 97.5% CI for the seroconversion rate (SCR) must be ≥ 40%; for each age subgroup, the LB of the 95% CI for the SCR must be ≥ 40%.
d %HI titer ≥ 1:40 is the percentage of subjects with an HI titer of at least 1:40. Success criteria for the %HI ≥ 1:40: For subjects 6 months through 17 years, the lower bound (LB) of the 97.5% CI for the % HI ≥40 must be ≥ 70%; For each age subgroup, the lower bound (LB) of the 95% CI for the % HI ≥40 must be ≥ 70%

15 REFERENCES

1. Lasky T, Terracciano GJ, Magder L, et al. The Guillain-Barre syndrome and the 1992-1993 and 1993-1994 influenza vaccines. N Engl J Med 1998; 339 (25): 1797-1802.
2. Hannoun C, Megas F, Piercy J. Immunogenicity and protective efficacy of influenza vaccination. Virus Res 2004; 103:133-138.
3. Hobson D, Curry RL, Beare A, et al. The role of serum hemagglutinin-inhibiting antibody in protection against challenge infection with influenza A2 and B viruses. J Hyg Camb 1972;767-777.

16 HOW SUPPLIED/STORAGE AND HANDLING

Information on the AUDENZ package presentation is provided in Table 9 below.

Table 9. AUDENZ Product Presentations
Presentation | Package size | Carton NDC Number | Description of Component and Component NDC Number
Pre-filled Syringe | 10 syringes per carton | 70461-700-03 | 0.5 mL single dose pre-filled syringe [NDC 70461-700-04]
Multi-dose Vial | 25 vials per carton | 70461-800-40 | 5 mL multi-dose vial [NDC 70461-800-41]

The tip caps and plungers of the pre-filled syringes and the multi-dose vial stopper are not made with natural rubber latex..

AUDENZ should be stored in a refrigerator at 2°C to 8°C (36°F to 46°F). Do not freeze. Discard if the vaccine has been frozen. Protect from light.

17 PATIENT COUNSELING INFORMATION

- Emphasize that it is important to complete the two-dose immunization series.
- Inform vaccine recipients, parents or guardians of the potential benefits and risks of immunization with AUDENZ.
- Educate vaccine recipients, parents or guardians of potential side effects and instruct them to report any adverse events to their healthcare provider and/or VAERs at 1-800-822-7967 or www.vaers.hhs.gov.
- Inform vaccine recipients, parents or guardians that AUDENZ contains non-infectious particles and cannot cause influenza.
- Inform vaccine recipients, parents or guardians that AUDENZ is intended to provide protection against illness due to influenza virus contained in the vaccine.

Manufactured by: Seqirus Inc. 475 Green Oaks Parkway, Holly Springs, NC 27540, U.S.A.

U.S. License No. 2049

Distributed by: Seqirus USA Inc. 25 Deforest Avenue, Summit NJ 07901, U.S.A
1-855-358-8966

AUDENZ™, FLUCELVAX®, FLUCELVAX® QUADRIVALENT and MF59® are owned by or licensed to Seqirus UK Limited or its affiliates.

Principal Display Panel – Syringe Label

Influenza A (H5N1) Monovalent
Vaccine, Adjuvanted

AUDENZ™

NDC 70461-700-04

Principal Display Panel – Carton Label

NDC 70471-700-03

For use in person 6 months of age and older

For Intramuscular Injection Only

Ten 0.5 mL, single-dose, pre-filled syringes

Rx Only

Influenza A (H5N1)
Monovalent Vaccine,
Adjuvanted

AUDENZ™

Seqirus™

PACKAGE LABEL

Principal Display Panel - 5 mL Multi Dose Vial Label

NDC 70461-800-41

Influenza A (H5N1)
Monovalent Vaccine,
Adjuvanted
AUDENZ™

5 mL Multi-dose Vial

FOR IM USE ONLY

Rx Only

For use in persons 6 months of
age and older.

Dose: 0.5 mL (see package insert)

Store between 2 – 8°C (36 – 46°F)

DO NOT FREEZE

US License No. 2049

Manufactured by Seqirus Inc.

Holly Springs, NC 27540, USA

Distributed by Seqirus USA Inc.

Summit, NJ 07901, USA

Principal Display Panel - 5 mL Carton Label

NDC 70461-800-40

Influenza A (H5N1)
Monovalent Vaccine,
Adjuvanted
AUDENZ™

Twenty-five 5 mL Multi-dose Vials.

Ten doses per vial.

For Intramuscular Injection Only.

Shake gently before use.

For use in persons 6 months of age and older.

Dosage: 0.5 mL equals one dose. Give two doses, 21 days apart.

See prescribing information for additional details.

Store between 2 – 8°C (36 – 46°F). Do not freeze.

Discard if the vaccine has been frozen. Protect from light.